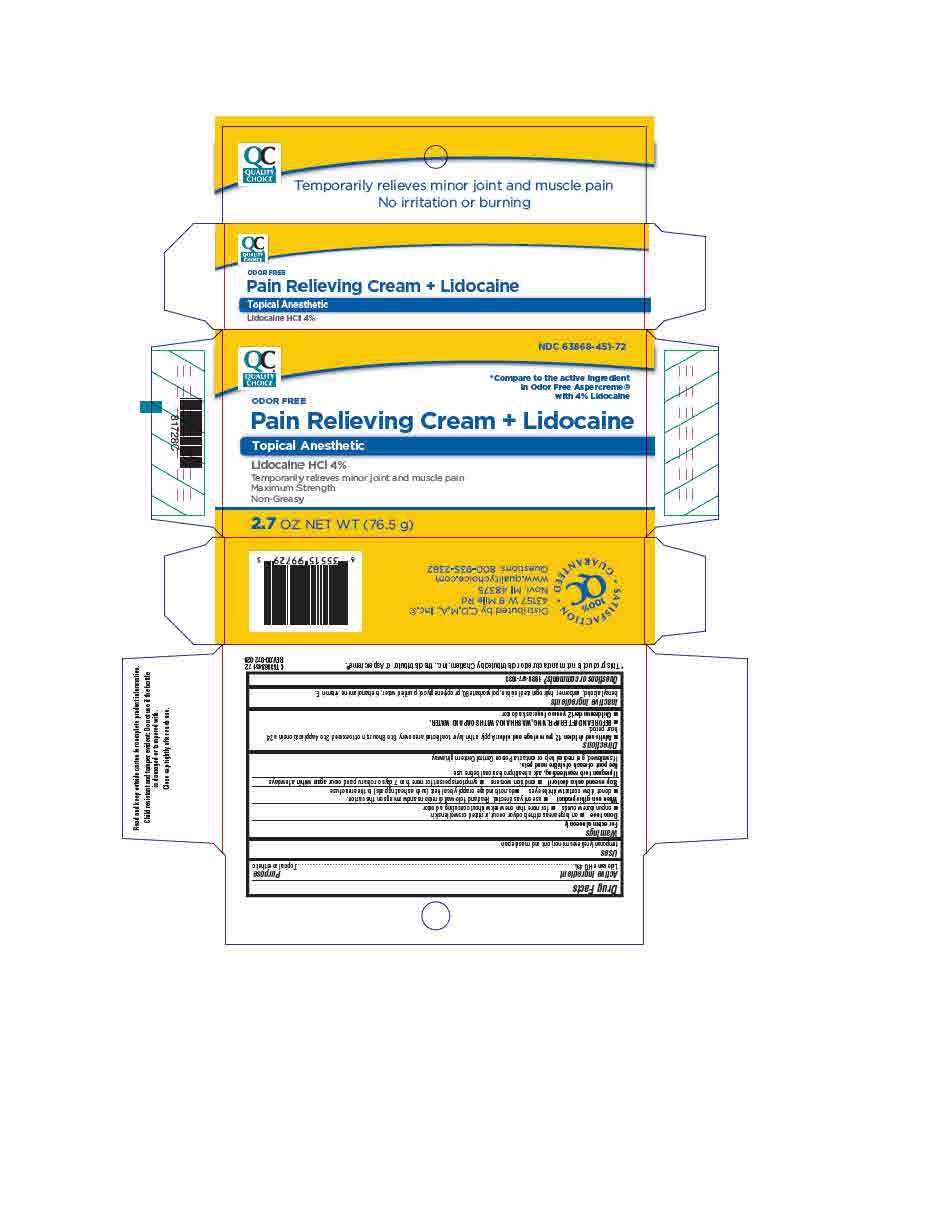 DRUG LABEL: Lidocaine HCl 4%
NDC: 63868-451 | Form: OINTMENT
Manufacturer: CHAIN DRUG MARKETING ASSOCIATION INC
Category: otc | Type: HUMAN OTC DRUG LABEL
Date: 20220412

ACTIVE INGREDIENTS: LIDOCAINE HYDROCHLORIDE 4 g/100 g
INACTIVE INGREDIENTS: .ALPHA.-TOCOPHEROL ACETATE, DL-; WATER; POLYSORBATE 80; LECITHIN, SOYBEAN; BENZYL ALCOHOL; CARBOMER 940; PROPYLENE GLYCOL; TROLAMINE

QC Pain Relieving Cream + Lidocaine
Lidocaine HCl 4%

ACTIVE INGREDIENT

Lidocaine HCl 4%

INACTIVE INGREDIENT

benzyl alcohol, carbomer, hydrogenated lecithin, polysorbate 80, propylene glycol, purified water, triethanolamine, vitamin E

DOSAGE AND ADMINISTRATION

Adults and children 12 years and older: apply a thin layer to affected area every 6 to 8 hours, not to exceed 3 to 4 applications in a 24-hour period.

BEFORE AND AFTER APPLYING, WASH HANDS WITH SOAP AND WATER.

Children under 12 years: ask a doctor

INDICATIONS AND USAGE

temporary relieves minor joint and muscle pain

WARNINGS

For external use only

Do not use on large areas of the body or on cut, irritated or swollen skin, on puncture wounds, for more than one week without consulting a doctor.

When using this product use only as directed. Read and follow all directions and warnings on this carton, do not allow contact with the eyes, do not bandage or apply local heat (such as heating pads) to the area of use.

Stop use and ask a doctor if condition worsens, symptoms persist for more than 7 days or clear up and occur again within a few days.

If pregnant or breast-feeding, ask a health professional before use.

Keep out of reach of children and pets.

If swallowed, get medical help or contact a Poison Control Center right away.

Keep out of reach of children and pets.

If swallowed, get medical help or contact a Poison Control Center right away.

PURPOSE

Topical anesthetic